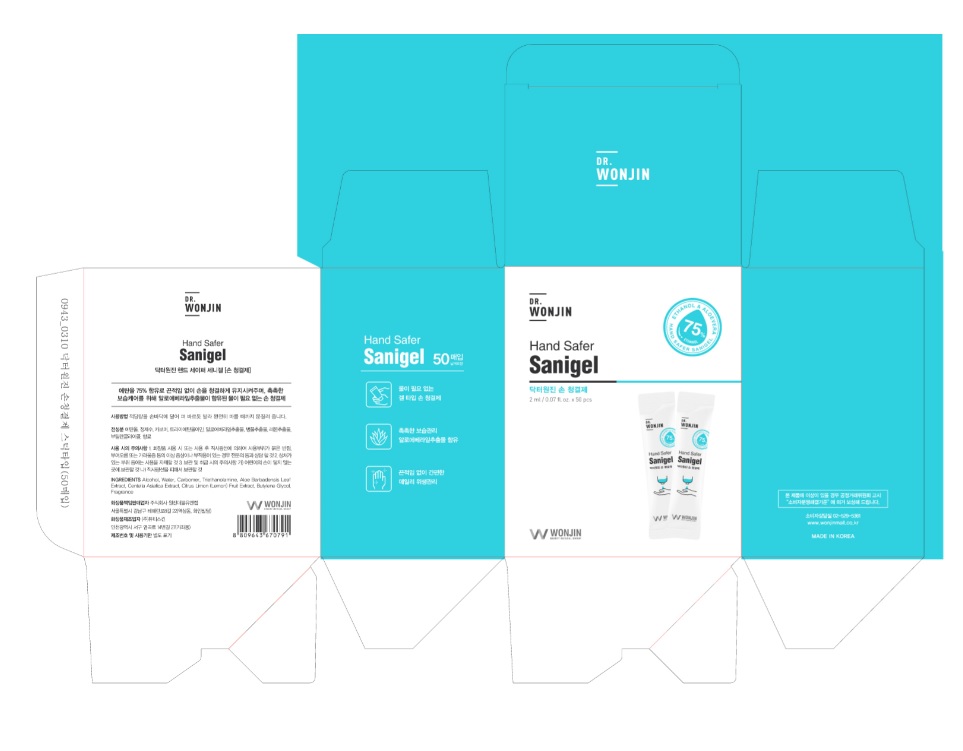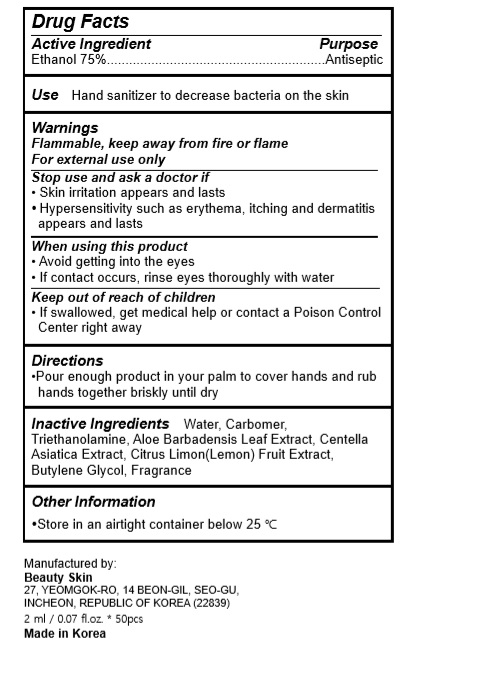 DRUG LABEL: DR. WONJIN Hand Safer Sanigel
NDC: 75708-7502 | Form: GEL
Manufacturer: BEAUTY SKIN.CO.,Ltd.
Category: otc | Type: HUMAN OTC DRUG LABEL
Date: 20200509

ACTIVE INGREDIENTS: ALCOHOL 1.5 mL/2 mL
INACTIVE INGREDIENTS: LEMON; BUTYLENE GLYCOL; ALOE VERA LEAF; CARBOMER HOMOPOLYMER, UNSPECIFIED TYPE; WATER; TROLAMINE; CENTELLA ASIATICA

DR. WONJIN Hand Safer Sanigel
2 ml x 50 pces